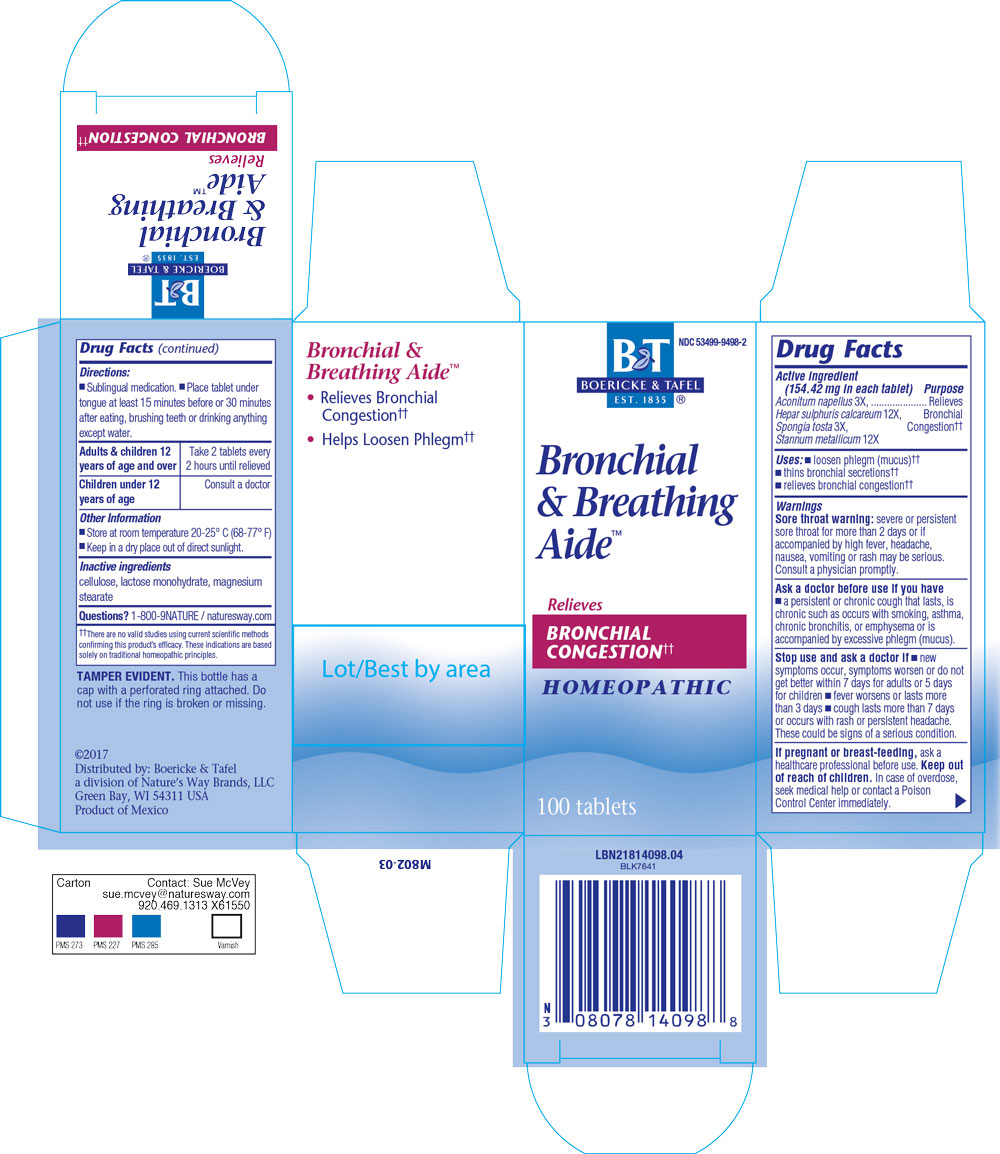 DRUG LABEL: Bronchial and Breathing Aide
NDC: 53499-9498 | Form: TABLET
Manufacturer: Schwabe North America, Inc
Category: homeopathic | Type: HUMAN OTC DRUG LABEL
Date: 20220726

ACTIVE INGREDIENTS: ACONITUM NAPELLUS 3 [hp_X]/1 1; CALCIUM SULFIDE 12 [hp_X]/1 1; SPONGIA OFFICINALIS SKELETON, ROASTED 3 [hp_X]/1 1; Tin 12 [hp_X]/1 1
INACTIVE INGREDIENTS: LACTOSE MONOHYDRATE; MAGNESIUM STEARATE; CELLULOSE, MICROCRYSTALLINE

Bronchial and Breathing Aide

Active Ingredients

Aconitum napellus 3X

Hepar sulphuris calcareum 12X

Spongia tosta 3X

Stannum metallicum 12X

Inactive Ingredients

Cellulose

Lactose monohydrate

Magnesium stearate

Purpose

Loosen phlegm (mucus),

thins bronchial secretions,

relieves bronchial congestion

Indications & Usage

Loosen phlegm (mucus),

thins bronchial secretions,

relieves bronchial congestion

Dosage & Administration

Sublingual mediation.

Place tablet under tonge at least 15 minutes before or 30 minutes after eating, brushing teeth or drinking anything except water.

Adults & Children 12 years of age and over: Take 2 tablets every 2 hours until relieved

Children under 12 years of age: Consult a doctor

Warning

Sore Throat Warning: severe or persistent sore throat for more than 2 days or if accompanied by high fever, headache, nausea, vomiting or rash may be serious.

Consult a physician promptly.

Ask Doctor

Ask a doctor before use if you have a persistent or chronic cough that lasts, is chronic such as occurs with smoking, asthma, chronic bronchitis, or emphysema or is accompanied by excessive phlegm (mucus).

Stop Use

Stop use and ask a doctor if new symptoms occur, symptoms worsen or do not get better within 7 days for adults or 5 days for children, fever worsens or lasts more than 3 days, cough lasts more than 7 days or occurs with rash or persistent headache. These could be signs of a serious condition.

Pregnancy or Breast Feeding

If pregnant or breast-feeding, ask a healthcare professional before use.

Keep out of reach of children

Keep out of the reach of children.

Overdosage

In case of overdose, seek medical help or contact a Poison Control Center immediately.